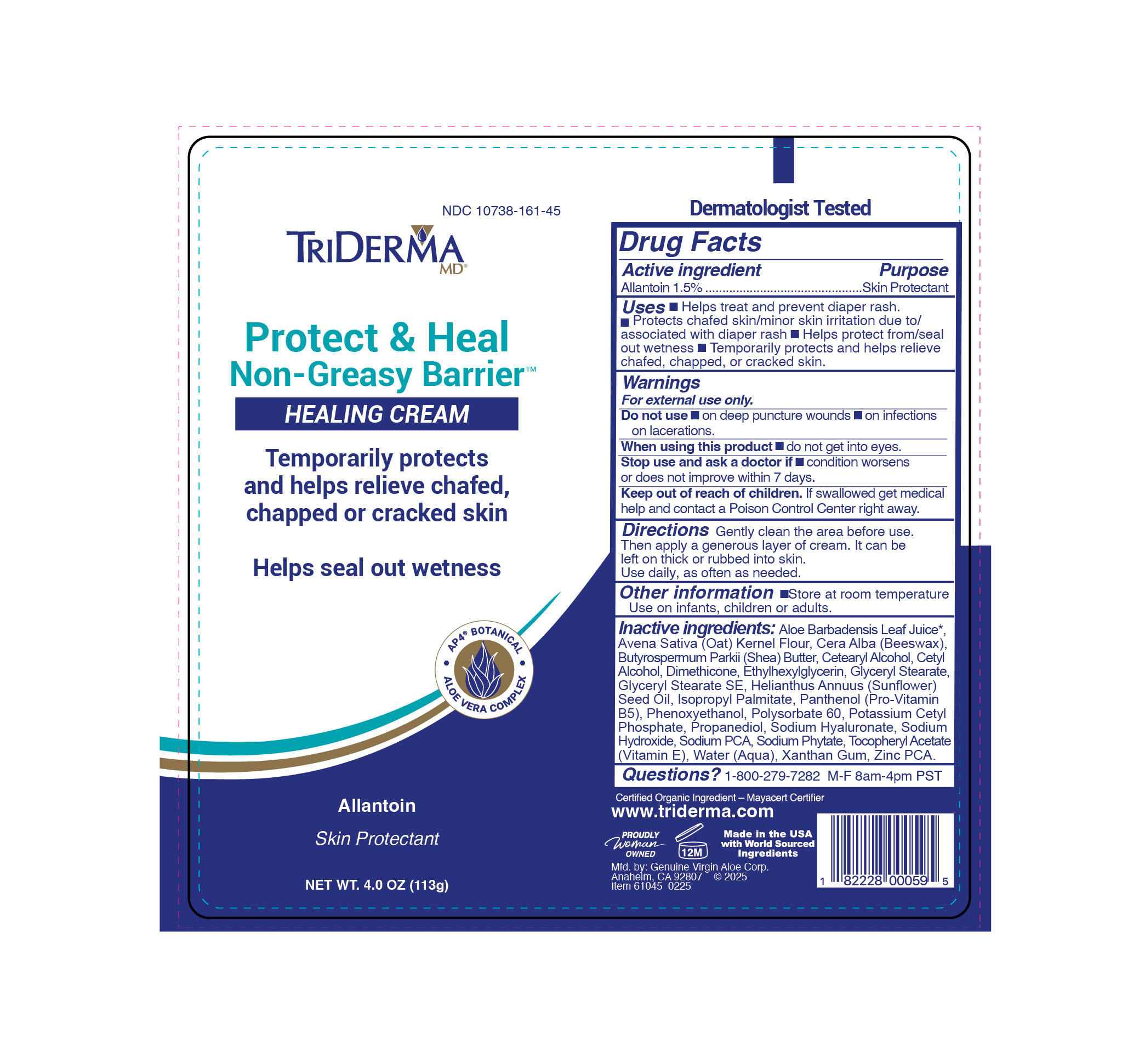 DRUG LABEL: TriDerma Protect Heal Non Greasy Barrier Cream
NDC: 10738-161 | Form: CREAM
Manufacturer: Genujine Virgin Aloe Corporation
Category: otc | Type: HUMAN OTC DRUG LABEL
Date: 20260129

ACTIVE INGREDIENTS: ALLANTOIN 1.5 g/100 g
INACTIVE INGREDIENTS: DIMETHICONE 100; BEESWAX; ALOE VERA LEAF JUICE; SHEA BUTTER

TriDerma Protect Heal Non Greasy Barrier Cream

ACTIVE INGREDIENT

Allantoin 1.5%

PURPOSE

Skin Protectant

INDICATIONS AND USAGE

helps treat and prevent diaper rash, protects chafed skin, minor skin irritation due to / associated with diaper rash, helps protects from / seal out wetness, temporarily protects and helps relieved chafed, chapped or cracked skin.

WARNINGS

for external use only

DO NOT USE

on deep puncture wounds, on infections, on lacerations

WHEN USING

do not get into eyes

stop use and ask a doctor if condition worsens or does not improve within 7 days.

KEEP OUT OF REACH OF CHILDREN

if swallowed get medical help and contact a Poison Control Center right away.

DOSAGE AND ADMINISTRATION

gently clean the area beforfe use. then apply a generous layer of cream. it can be left on thick or rubbed into skin. use daily, as often as needed.

INACTIVE INGREDIENT

Aloe Barbadensis Leaf Juice*,
Avena Sativa (Oat) Kernel Flour, Cera Alba (Beeswax),
Butyrospermum Parkii (Shea) Butter, Cetearyl Alcohol, Cetyl
Alcohol, Dimethicone, Ethylhexylglycerin, Glyceryl Stearate,
Glyceryl Stearate SE, Helianthus Annuus (Sunflower) Seed
Oil, Isopropyl Palmitate, Panthenol (Pro-Vitamin B5),
Phenoxyethanol, Polysorbate 60, Potassium Cetyl
Phosphate, Propanediol, Sodium Hyaluronate, Sodium
Hydroxide, Sodium PCA, Sodium Phytate, Tocopheryl
Acetate (Vitamin E), Water (Aqua), Xanthan Gum, Zinc PCA.

*Certified Organic Ingredient - Mayacert Certifier